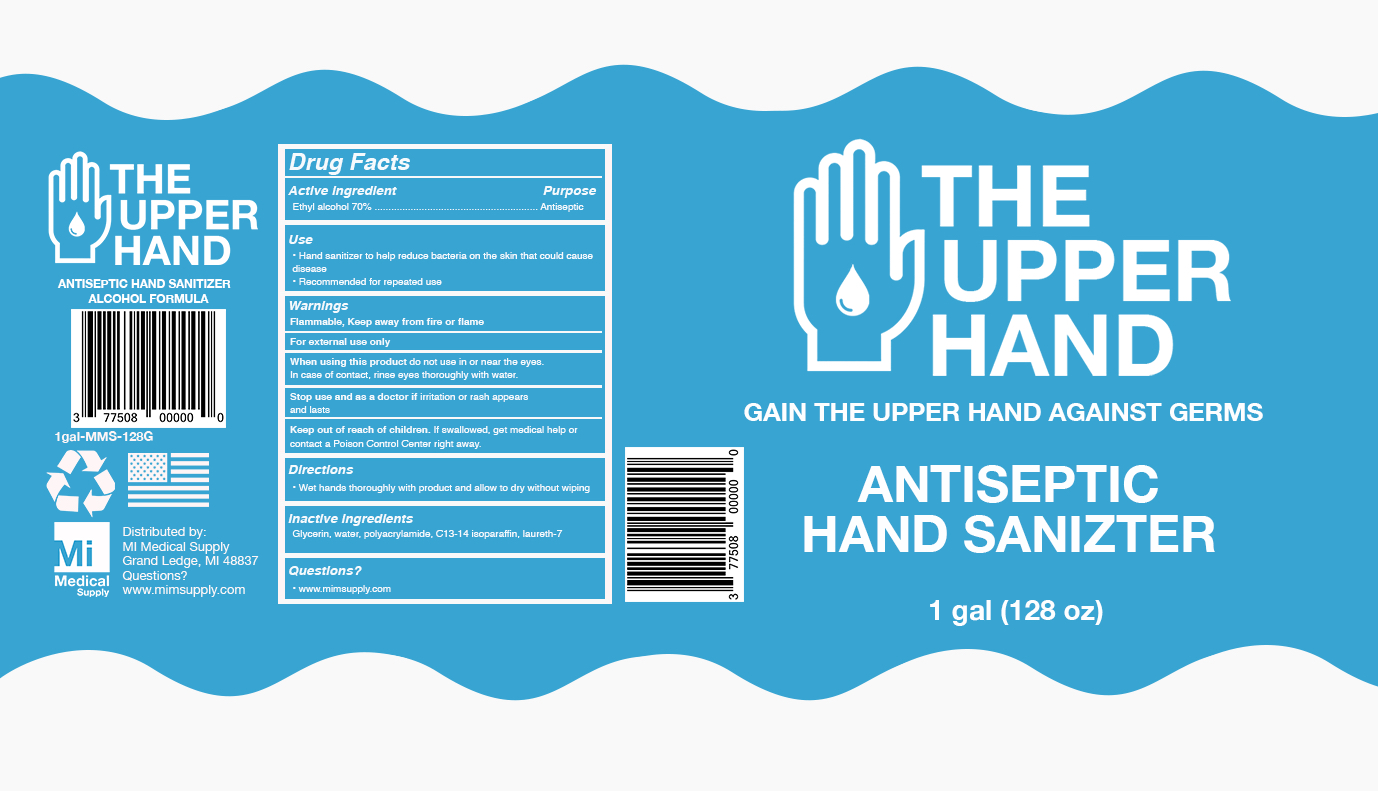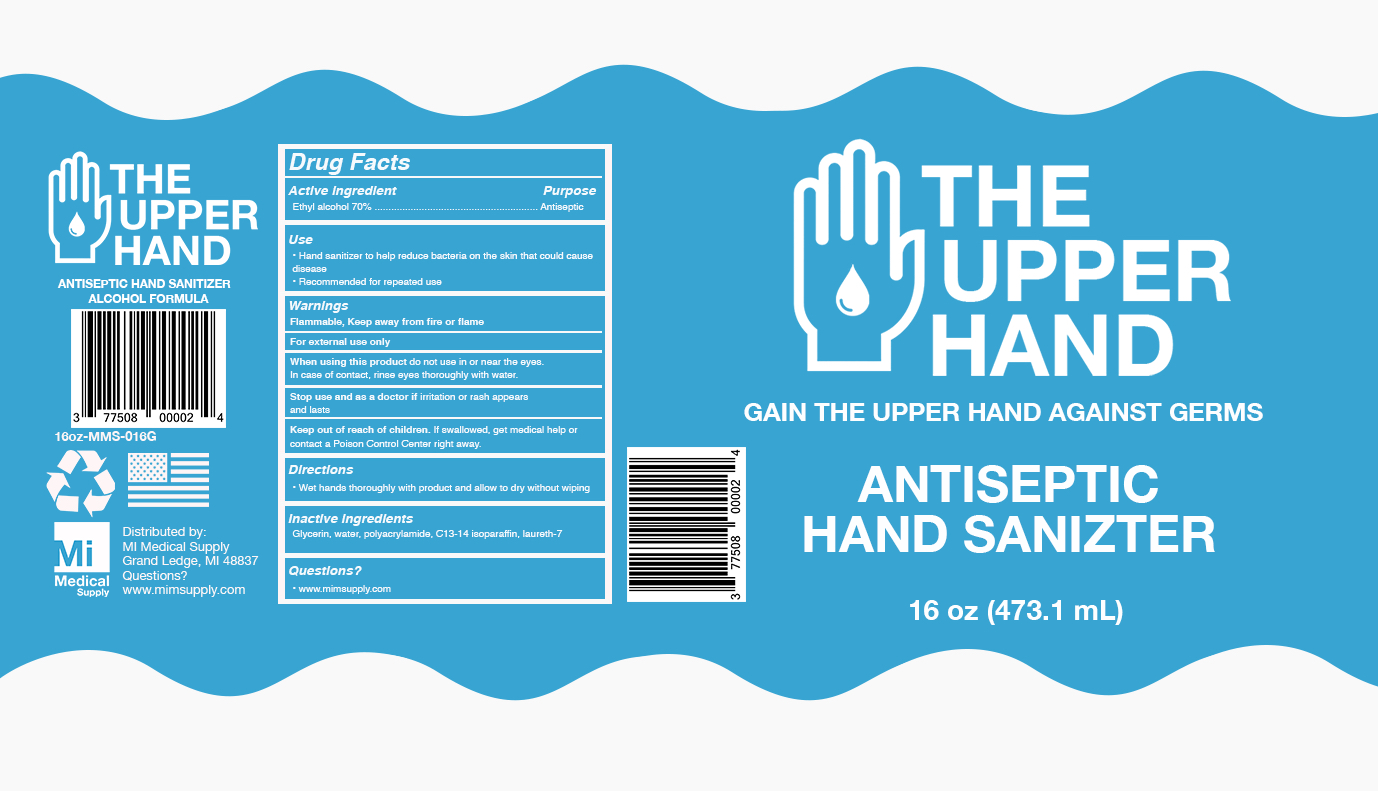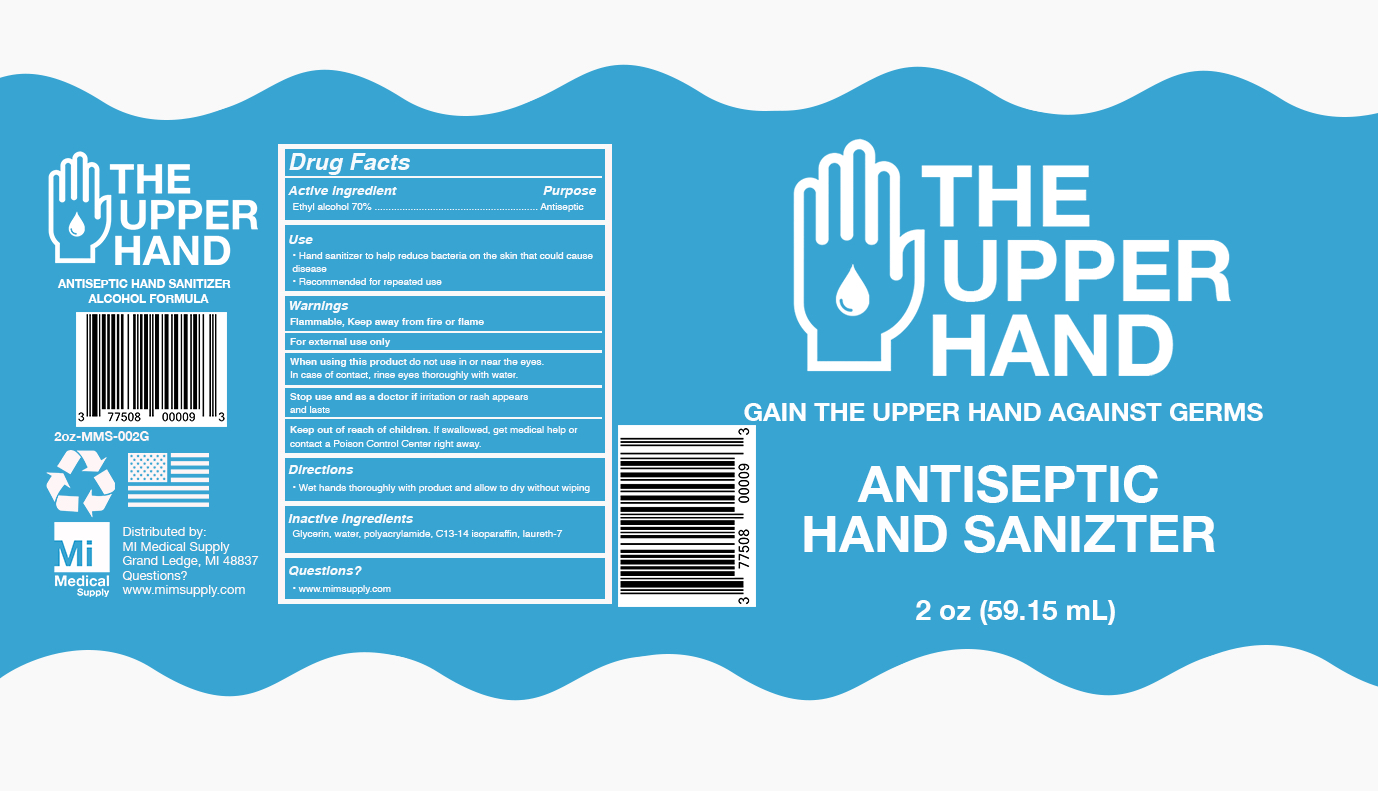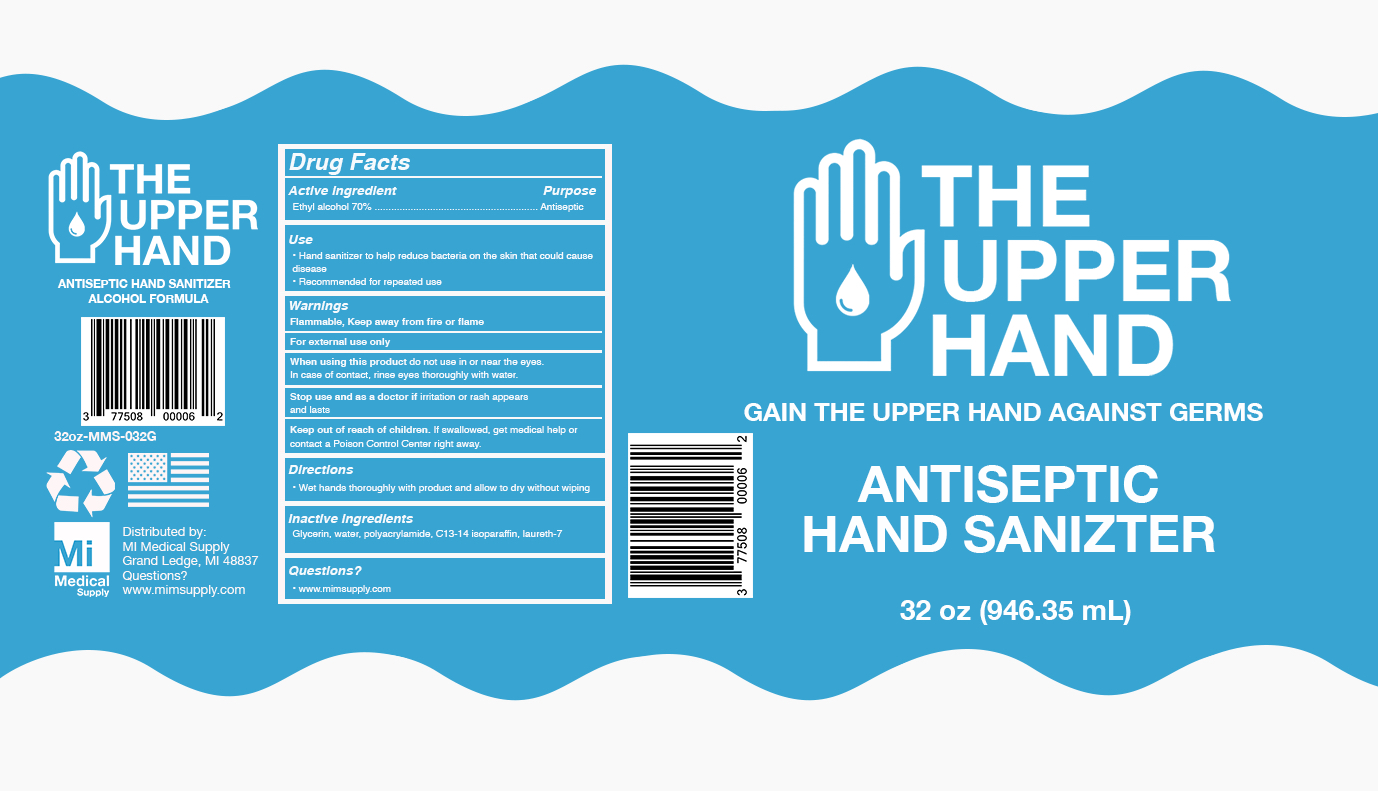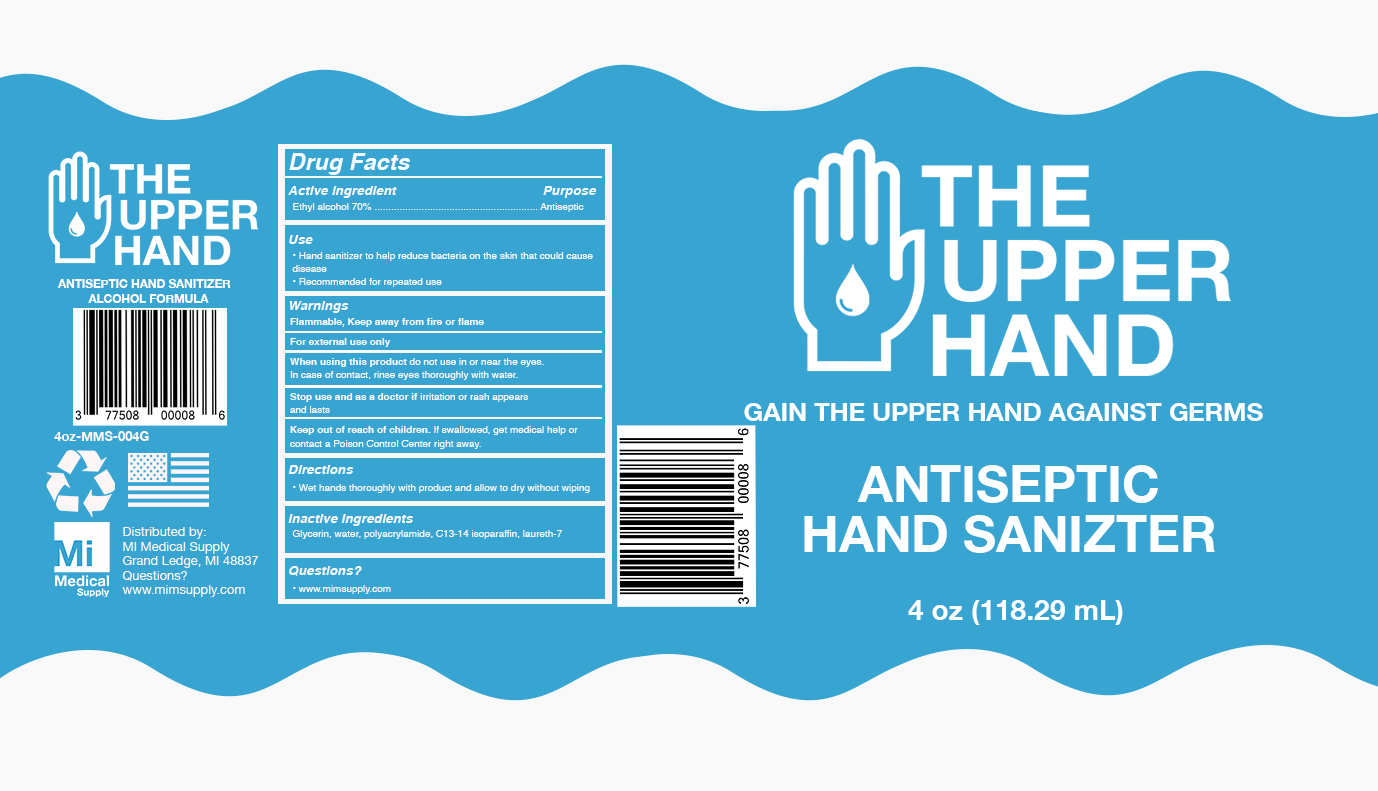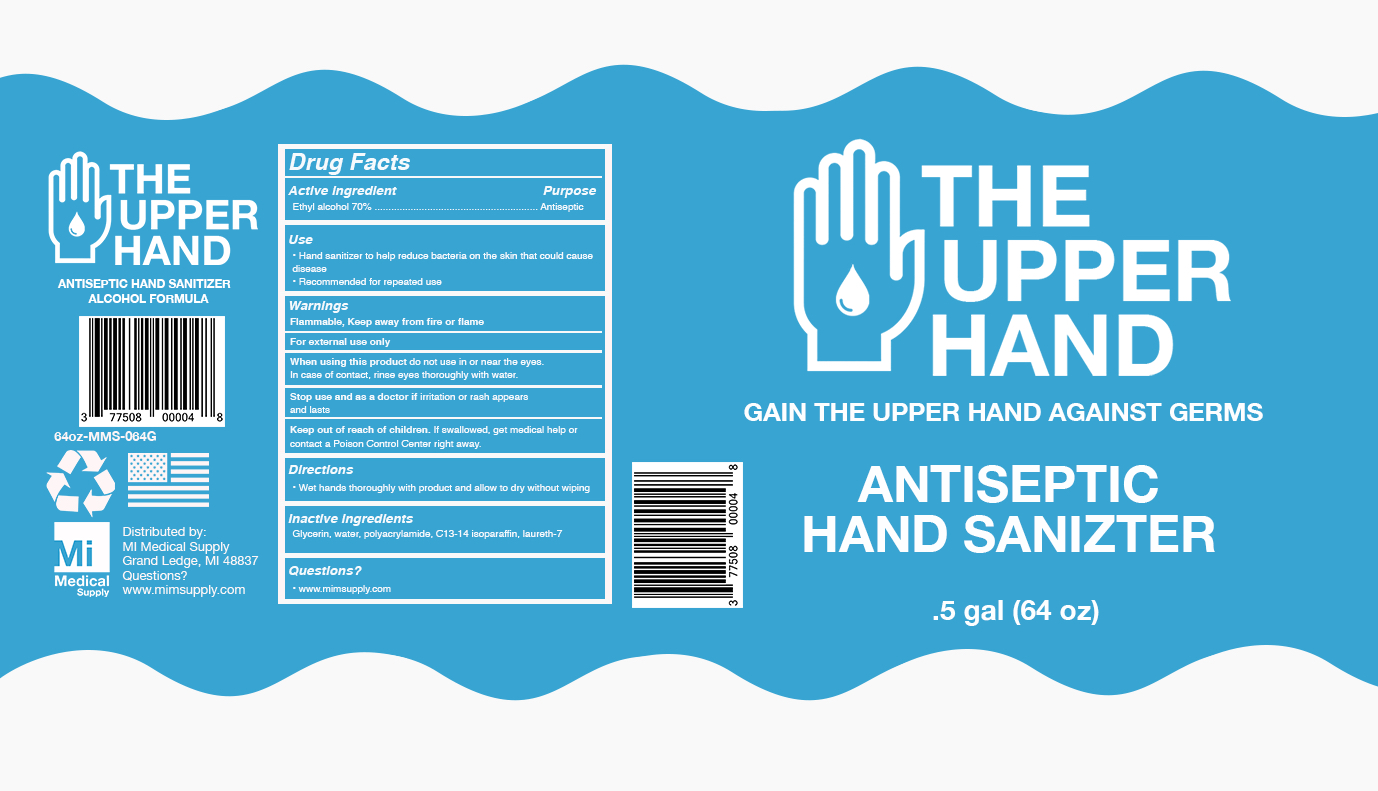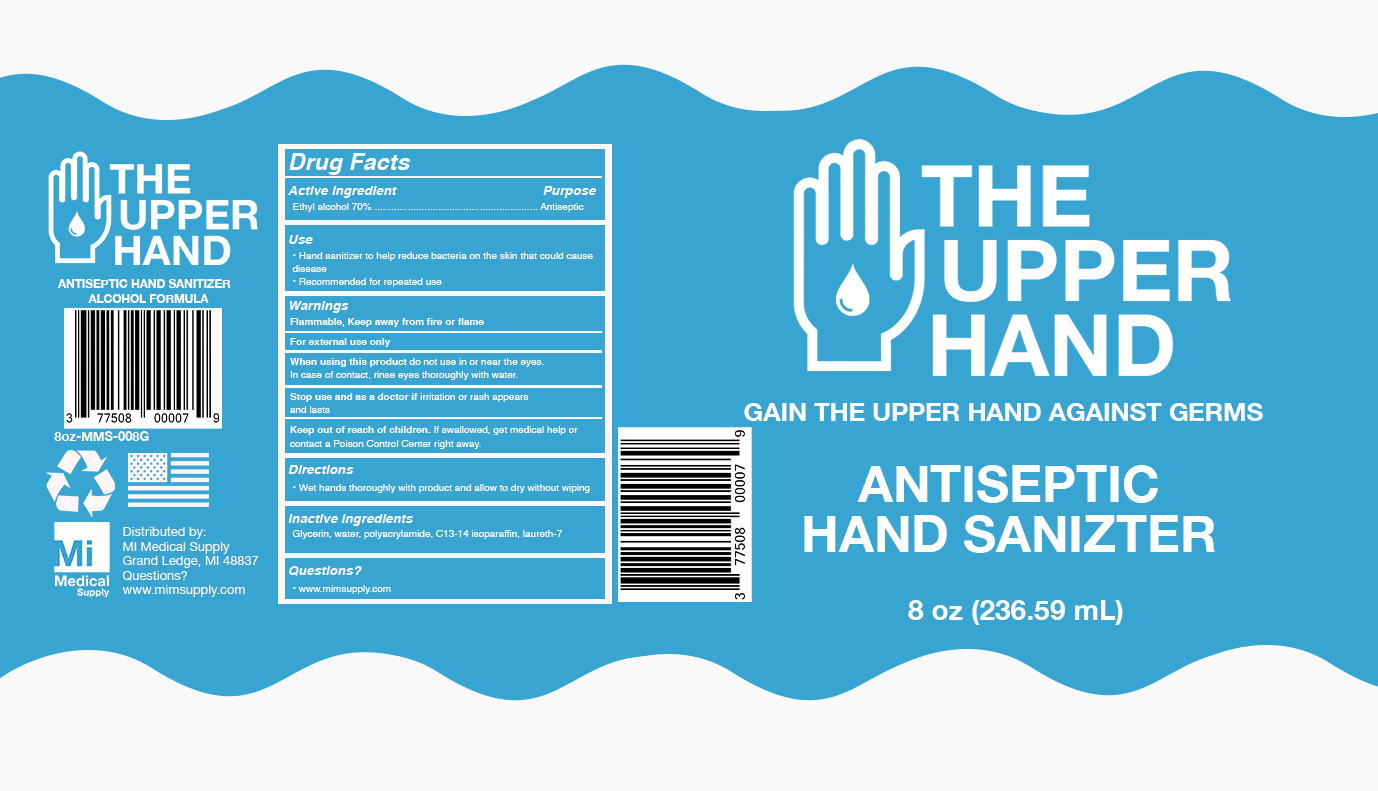 DRUG LABEL: The Upper Hand
NDC: 77508-101 | Form: GEL
Manufacturer: MI Medical Supply
Category: otc | Type: HUMAN OTC DRUG LABEL
Date: 20200603

ACTIVE INGREDIENTS: ALCOHOL 70 mL/100 mL
INACTIVE INGREDIENTS: WATER 26.6 mL/100 mL; SODIUM ACRYLOYLDIMETHYLTAURATE-ACRYLAMIDE COPOLYMER (1:1; 90000-150000 MPA.S) 1.34 mL/100 mL; GLYCERIN 2.06 mL/100 mL

Gel Hand Sanitizer

The Upper Hand Gel Sanitizer

Drug Facts Box

Ethyl Alcohol 70%

Drug Facts Box OTC- Purpose Section

Antiseptic

Drug Facts Box OTC- Indications and Usage Section

Hand Sanitizer to help reduce bacteria on the skin that could cause disease.

Recommended for Repeated use

Drug Facts Box OTC - Warnings Section

Flammable, Keep away from fire or flame

For External Use Only

Drug Facts Box OTC- When Using Section

When using this product do not use in or near the eyes

In case of contact, rinse eyes thoroughly with water

Drug Facts Box OTC- Stop Use Section

Stop use and ask a doctor if irritation or rash appears and lasts

Drug Facts Box OTC- Keep out of reach of children section

Keep out of reach of children. If swallowed, get medical help or contact a poison control center right away.

Drug Facts Box OTC-Dosage and Administration Section

Wet hands thoroughly with product and allow to dry without wiping.

Drug Facts Box OTC- Inactive Ingredient Section

Glycerin, Water, Polyacrylamide, C13-14 Isoparrafin, Laureth-7